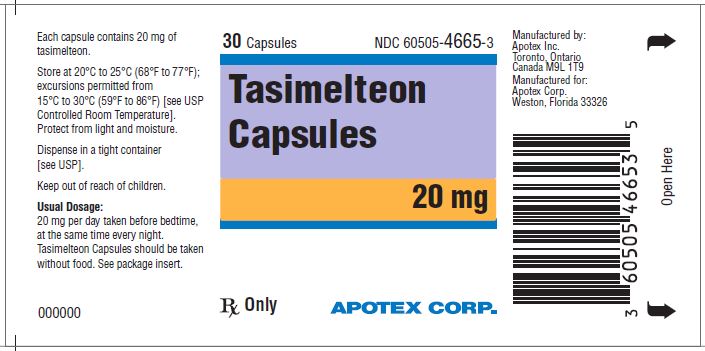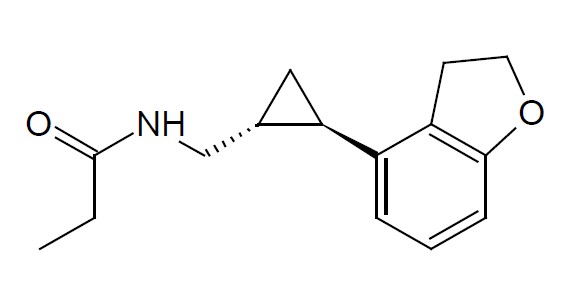 DRUG LABEL: Tasimelteon
NDC: 60505-4665 | Form: CAPSULE
Manufacturer: Apotex Corp.
Category: prescription | Type: HUMAN PRESCRIPTION DRUG LABEL
Date: 20250410

ACTIVE INGREDIENTS: Tasimelteon 20 mg/1 1
INACTIVE INGREDIENTS: SILICON DIOXIDE; Croscarmellose Sodium; Magnesium Stearate; MICROCRYSTALLINE CELLULOSE; Fd&C Blue No. 1; Fd&C Red No. 3; Fd&C Yellow No. 6; GELATIN, UNSPECIFIED; Titanium Dioxide; POVIDONE, UNSPECIFIED; PROPYLENE GLYCOL; Shellac; Sodium Hydroxide

HIGHLIGHTS OF PRESCRIBING INFORMATION

These highlights do not include all the information needed to use TASIMELTEON CAPSULES safely and effectively. See full prescribing information for TASIMELTEON CAPSULES.
TASIMELTEON capsules, for oral use
Initial U.S. Approval: 2014

1 INDICATIONS AND USAGE

Tasimelteon capsules are a melatonin receptor agonist.

Tasimelteon capsules are indicated for the treatment of

- Non 24-Hour Sleep-Wake Disorder (Non-24) in adults (1)

2 DOSAGE AND ADMINISTRATION

Indicated Population | Dosage Form | Body Weight | Recommended Dosage
Non-24 (2.2)
Adults | Capsules | Not applicable | 20 mg one hour prior to bedtime

- Tasimelteon capsules and tasimelteon oral suspension are not substitutable (2.1)
- Administer at the same time every night (2.2)
- Take without food (2.4)

3 DOSAGE FORMS AND STRENGTHS

Capsules: 20 mg (3)

4 CONTRAINDICATIONS

None (4)

5 WARNINGS AND PRECAUTIONS

May cause somnolence: After taking tasimelteon capsules, patients should limit their activity to preparing for going to bed, because tasimelteon capsules can impair the performance of activities requiring complete mental alertness (5.1)

6 ADVERSE REACTIONS

The most common adverse reactions (incidence >5% and at least twice as high on tasimelteon than on placebo) were headache, increased alanine aminotransferase, nightmares or unusual dreams, and upper respiratory or urinary tract infection (6.1)

To report SUSPECTED ADVERSE REACTIONS, contact Apotex Corp. at 1-800-706-5575 or FDA at 1-800-FDA-1088 or www.fda.gov/medwatch.

7 DRUG INTERACTIONS

- Strong CYP1A2 inhibitors (e.g., fluvoxamine): Avoid use of tasimelteon in combination with strong CYP1A2 inhibitors because of increased exposure (7.1, 12.3)
- Strong CYP3A4 inducers (e.g., rifampin): Avoid use of tasimelteon in combination with rifampin or other CYP3A4 inducers, because of decreased exposure (7.2, 12.3)

8 USE IN SPECIFIC POPULATIONS

- Hepatic impairment: Tasimelteon has not been studied in patients with severe hepatic impairment and is not recommended in these patients (8.6)

FULL PRESCRIBING INFORMATION

1 INDICATIONS AND USAGE

1.1 Non-24-Hour Sleep-Wake Disorder (Non-24)

Tasimelteon capsules are indicated for the treatment of Non-24 in adults.

2 DOSAGE AND ADMINISTRATION

2.1 Non-Interchangeability between Tasimelteon Capsules and Tasimelteon Oral Suspension

Tasimelteon capsules and tasimelteon oral suspension are not substitutable [see Clinical Pharmacology (12.3)].

2.2 Recommended Dosage for Tasimelteon Capsules for Non-24

Adults

The recommended dosage of tasimelteon capsules in adults is 20 mg one hour before bedtime, at the same time every night.

Because of individual differences in circadian rhythms, drug effect may not occur for weeks or months.

2.4 Important Administration Information

Administer tasimelteon capsules without food [see Clinical Pharmacology (12.3)].

If a patient is unable to take tasimelteon capsules at approximately the same time on a given night, they should skip that dose and take the next dose as scheduled.

3 DOSAGE FORMS AND STRENGTHS

Capsules: 20 mg hard gelatin capsule with dark blue, opaque body and dark blue, opaque cap. Imprinted “APO” and “TAS” over “20” in white ink.

4 CONTRAINDICATIONS

None.

5 WARNINGS AND PRECAUTIONS

5.1 Somnolence

After taking tasimelteon capsules, patients should limit their activity to preparing for going to bed. Tasimelteon capsules can potentially impair the performance of activities requiring complete mental alertness.

6 ADVERSE REACTIONS

6.1 Clinical Trials Experience

Because clinical trials are conducted under widely varying conditions, adverse reaction rates observed in the clinical trials of a drug cannot be directly compared to rates in the clinical trials of another drug and may not reflect the rates observed in clinical practice.

More than 2080 subjects have been treated with at least one dose of tasimelteon, of which more than 380 have been treated for > 26 weeks and more than 170 have been treated for > 1 year.

Non-24-Hour Sleep-Wake Disorder (Non-24)

A 26-week, parallel-arm placebo-controlled study (Study 1) evaluated tasimelteon (n=42) compared to placebo (n=42) in patients with Non-24. A randomized-withdrawal, placebo-controlled study of 8 weeks duration (Study 2) also evaluated tasimelteon (n=10), compared to placebo (n=10), in patients with Non-24.

In placebo-controlled studies, 6% of patients exposed to tasimelteon discontinued treatment due to an adverse event, compared with 4% of patients who received placebo.

Table 2 shows the incidence of adverse reactions from Study 1.

Table 2: Adverse Reactions in Study 1

 | Tasimelteon N=42 | Placebo N=42
Headache | 17 % | 7 %
Alanine aminotransferase increased | 10 % | 5 %
Nightmare/abnormal dreams | 10 % | 0 %
Upper respiratory tract infection | 7 % | 0 %
Urinary tract infection | 7 % | 2 %

*Adverse reactions with an incidence > 5% and at least twice as high on tasimelteon than on placebo are displayed.

7 DRUG INTERACTIONS

7.1 Strong CYP1A2 Inhibitors (e.g., fluvoxamine)

Avoid use of tasimelteon in combination with fluvoxamine or other strong CYP1A2 inhibitors because of a potentially large increase in tasimelteon exposure and greater risk of adverse reactions [see Clinical Pharmacology (12.3)].

7.2 Strong CYP3A4 Inducers (e.g., rifampin)

Avoid use of tasimelteon in combination with rifampin or other CYP3A4 inducers because of a potentially large decrease in tasimelteon exposure with reduced efficacy [see Clinical Pharmacology (12.3)].

7.3 Beta-Adrenergic Receptor Antagonists (e.g., acebutolol, metoprolol)

Beta-adrenergic receptor antagonists have been shown to reduce the production of melatonin via specific inhibition of beta-1 adrenergic receptors. Nighttime administration of beta-adrenergic receptor antagonists may reduce the efficacy of tasimelteon.

8 USE IN SPECIFIC POPULATIONS

8.1 Pregnancy

Risk Summary

Available postmarketing case reports with tasimelteon use in pregnant women are not sufficient to evaluate drug-associated risk of major birth defects, miscarriage or adverse maternal or fetal outcomes. In pregnant rats, no embryofetal developmental toxicity was observed at exposures of 50 mg/kg/day, or up to 24 times higher than the human exposure at the maximum recommended human dose (MRHD) (see Data).

The estimated background risk of major birth defects and miscarriage for the indicated populations are unknown. In the U.S. general population, the estimated background risk of major birth defects and miscarriage in clinically recognized pregnancies is 2% to 4% and 15% to 20%, respectively.

Data

Animal Data

In pregnant rats administered tasimelteon at oral doses of 5, 50, or 500 mg/kg/day during the period of organogenesis, there were no effects on embryofetal development. The highest dose tested is approximately 240 times the MRHD of 20 mg/day, based on mg/m^2 body surface area.

In pregnant rabbits administered tasimelteon at oral doses of 5, 30, or 200 mg/kg/day during the period of organogenesis, embryolethality and embryofetal toxicity (reduced fetal body weight and delayed ossification) were observed at the highest dose tested. The highest dose is approximately 200 times the MRHD.

Oral administration of tasimelteon at 50, 150, or 450 mg/kg/day to rats throughout organogenesis resulted in persistent reductions in body weight, delayed sexual maturation, and physical development, and neurobehavioral impairment in offspring at the highest dose tested which is approximately 220 times the MRHD based on mg/m^2 body surface area. Reduced body weight in offspring was also observed at the mid-dose. The no effect dose (NOEL), (50 mg/kg/day) is approximately 25 times the MRHD based on mg/m^2 body surface area.

8.2 Lactation

Risk Summary

There are no data on the presence of tasimelteon or its metabolites in human or animal milk, the effects on the breastfed infant, or the effects on milk production. The developmental and health benefits of breastfeeding should be considered along with the mother’s clinical need for tasimelteon and any potential adverse effects on the breastfed infant from tasimelteon or from the underlying maternal condition.

8.4 Pediatric Use

Safety and effectiveness of tasimelteon capsules for the treatment of Non-24 in pediatric patients have not been established.

Juvenile Animal Toxicity Data

Juvenile rats received oral doses of tasimelteon at 50, 150, or 450 mg/kg from weaning (day 21) through adulthood (day 90). These doses are approximately 12 to 108 times the maximum recommended human dose (MRHD) of 20 mg based on a mg/m^2 body surface area. Toxicity was observed mainly at the highest dose and included mortality (females only), tremors, unsteady gait, decrease in growth and development compared to controls. The former reflected as decreases in bone growth, bone mineral content, bone ossification, and a delay in attainment of sexual maturation. Tasimelteon had no effect on fertility, reproduction, or learning and memory. The No Observed Adverse Effect Level (NOAEL) is 150 mg/kg/day, which is approximately 178 times the MRHD based on AUC.

8.5 Geriatric Use

The risk of adverse reactions may be greater in elderly (>65 years) patients than younger patients because exposure to tasimelteon is increased by approximately 2-fold compared with younger patients.

8.6 Hepatic Impairment

Dose adjustment is not necessary in patients with mild or moderate hepatic impairment. Tasimelteon has not been studied in patients with severe hepatic impairment (Child-Pugh Class C). Therefore, tasimelteon is not recommended for use in patients with severe hepatic impairment [see Clinical Pharmacology (12.3)].

8.7 Smokers

Smoking causes induction of CYP1A2 levels. The exposure of tasimelteon in smokers was lower than in non-smokers and therefore the efficacy of tasimelteon may be reduced in smokers [see Clinical pharmacology (12.3)].

9 DRUG ABUSE AND DEPENDENCE

9.1 Controlled Substance

Tasimelteon is not a controlled substance under the Controlled Substances Act.

9.2 Abuse

Tasimelteon did not produce any abuse-related signals in animal behavioral studies. Rats did not self-administer tasimelteon, suggesting that the drug does not have rewarding properties. There were also no signs or symptoms indicative of abuse potential in clinical studies with tasimelteon.

9.3 Dependence

Discontinuation of tasimelteon in humans following chronic administration did not produce withdrawal signs. Tasimelteon does not appear to produce physical dependence.

10 OVERDOSAGE

There is limited premarketing clinical experience with the effects of an overdosage of tasimelteon. As with the management of any overdose, general symptomatic and supportive measures should be used, along with immediate gastric lavage where appropriate. Intravenous fluids should be administered as needed. Respiration, pulse, blood pressure, and other appropriate vital signs should be monitored, and general supportive measures employed.

While hemodialysis was effective at clearing tasimelteon and the majority of its major metabolites in patients with renal impairment, it is not known if hemodialysis will effectively reduce exposure in the case of overdose.

As with the management of any overdose, the possibility of multiple drug ingestion should be considered. Contact a poison control center for current information on the management of overdose.

11 DESCRIPTION

Tasimelteon is a melatonin receptor agonist, chemically designated as (1R-trans)-N-[[2-(2,3-Dihydrobenzofuran-4-yl)cycloprop-1-yl]methyl]propanamide, containing two chiral centers. The molecular formula is C15H19NO2, and the molecular weight is 245.32 g/mol. The structural formula is:

Tasimelteon is a white to off-white powder. It is very slightly soluble in cyclohexane, slightly soluble in water and freely soluble or very soluble in methanol, 95% ethanol, acetonitrile, isopropanol, propylene glycol and ethyl acetate.

Tasimelteon capsules are intended for oral administration. Each capsule contains 20 mg of tasimelteon and the following inactive ingredients: colloidal silicon dioxide, croscarmellose sodium, magnesium stearate, and microcrystalline cellulose. Each hard gelatin capsule consists of FD&C Blue #1, FD&C Red #3, and FD&C Yellow #6, gelatin and titanium dioxide. The imprinting ink consists of povidone, propylene glycol, shellac, sodium hydroxide and titanium dioxide.

12 CLINICAL PHARMACOLOGY

12.1 Mechanism of Action

The mechanism by which tasimelteon exerts its therapeutic effect in patients with Non-24 is unclear. However, tasimelteon is an agonist at melatonin MT1 and MT2 receptors which are thought to be involved in the control of circadian rhythms.

12.2 Pharmacodynamics

Tasimelteon is an agonist at MT1 and MT2 receptors with greater affinity for the MT2 as compared to the MT1 receptor (Ki = 0.304 nM and 0.07 nM, respectively). The major metabolites of tasimelteon have less than one-tenth of the binding affinity of the parent molecule for both the MT1 and MT2 receptors.

12.3 Pharmacokinetics

The pharmacokinetics of tasimelteon is linear over doses ranging from 3 to 300 mg (0.15 to 15 times the recommended daily dosage). The pharmacokinetics of tasimelteon and its metabolites did not change with repeated daily dosing.

Absorption

The absolute oral bioavailability is 38.3%. The peak concentration (Tmax) of tasimelteon capsule occurred approximately 0.5 to 3 hours after fasted oral administration.

Effect of food

When administered with a high-fat meal, the Cmax of tasimelteon was 44% lower than when given in a fasted state, and the median Tmax was delayed by approximately 1.75 hours. Therefore, tasimelteon capsules should be taken without food.

Distribution

The apparent oral volume of distribution of tasimelteon at steady state in young healthy subjects is approximately 59 to 126 L. At therapeutic concentrations, tasimelteon is about 90% bound to proteins.

Metabolism

Tasimelteon is extensively metabolized. Metabolism of tasimelteon consists primarily of oxidation at multiple sites and oxidative dealkylation resulting in opening of the dihydrofuran ring followed by further oxidation to give a carboxylic acid. CYP1A2 and CYP3A4 are the major isozymes involved in the metabolism of tasimelteon.

Phenolic glucuronidation is the major phase II metabolic route.

Major metabolites had 13-fold or less activity at melatonin receptors compared to tasimelteon.

Elimination

Following oral administration of radiolabeled tasimelteon, 80% of total radioactivity was excreted in urine and approximately 4% in feces, resulting in a mean recovery of 84%. Less than 1% of the dose was excreted in urine as the parent compound.

The observed mean elimination half-life for tasimelteon is 1.3 ± 0.4 hours. The mean terminal elimination half-life ± standard deviation of the main metabolites ranges from 1.3 ± 0.5 to 3.7 ± 2.2.

Repeated once daily dosing with tasimelteon does not result in changes in pharmacokinetic parameters or significant accumulation of tasimelteon.

Studies in Specific Populations

Elderly

In elderly subjects, tasimelteon exposure increased by approximately two-fold compared with non-elderly adults.

Gender

The mean overall exposure of tasimelteon was approximately 20 to 30% greater in female than in male subjects.

Race

The effect of race on exposure of tasimelteon was not evaluated.

Hepatic Impairment

The pharmacokinetic profile of a 20 mg dose of tasimelteon was compared among eight subjects with mild hepatic impairment (Child-Pugh Score ≥5 and ≤6 points), eight subjects with moderate hepatic impairment (Child-Pugh Score ≥7 and ≤9 points), and 13 healthy matched controls. Tasimelteon exposure was increased less than two-fold in subjects with moderate hepatic impairment. Therefore, no dose adjustment is needed in patients with mild or moderate hepatic impairment. Tasimelteon has not been studied in patients with severe hepatic impairment (Child-Pugh Class C) and is not recommended in these patients.

Renal Impairment

The pharmacokinetic profile of a 20 mg dose of tasimelteon was compared among eight subjects with severe renal impairment (estimated glomerular filtration rate [eGFR] ≤ 29 mL/min/1.73m^2), eight subjects with end-stage renal disease (ESRD) (GFR < 15 mL/min/1.73m^2) requiring hemodialysis, and sixteen healthy matched controls. There was no apparent relationship between tasimelteon CL/F and renal function, as measured by either estimated creatinine clearance or eGFR. Subjects with severe renal impairment had a 30% lower clearance, and clearance in subjects with ESRD was comparable to that of healthy subjects. No dose adjustment is necessary for patients with renal impairment.

Smokers (smoking is a moderate CYP1A2 inducer)

Tasimelteon exposure decreased by approximately 40% in smokers, compared to non-smokers [see Use in Specific Populations (8.7)].

Drug Interaction Studies

No potential drug interactions were identified in in vitro studies with CYP inducers or inhibitors of CYP1A1, CYP1A2, CYP2B6, CYP2C9/2C19, CYP2E1, CYP2D6, and transporters including P-glycoprotein, OATP1B1, OATP1B3, OCT2, OAT1, and OAT3.

Effect of Other Drugs on Tasimelteon

Drugs that inhibit CYP1A2 and CYP3A4 are expected to alter the metabolism of tasimelteon.

Fluvoxamine (strong CYP1A2 inhibitor): the AUC0-inf and Cmax of tasimelteon increased by 7-fold and 2-fold, respectively, when co-administered with fluvoxamine 50 mg (after 6 days of fluvoxamine 50 mg per day) [see Drug Interactions (7.1)].

Ketoconazole (strong CYP3A4 inhibitor): tasimelteon exposure increased by approximately 50% when co-administered with ketoconazole 400 mg (after 5 days of ketoconazole 400 mg per day) [see Drug Interactions (7.2)].

Rifampin (strong CYP3A4 and moderate CYP2C19 inducer): the exposure of tasimelteon decreased by approximately 90% when co-administered with rifampin 600 mg (after 11 days of rifampin 600 mg per day). Efficacy may be reduced when tasimelteon is used in combination with strong CYP3A4 inducers, such as rifampin [see Drug Interactions (7.2)].

Effect of Tasimelteon on Other Drugs

Midazolam (CYP3A4 substrate): Administration of tasimelteon capsules 20 mg once a day for 14 days did not produce any significant changes in the Tmax, Cmax, or AUC of midazolam or 1-OH midazolam. This indicates there is no induction of CYP3A4 by tasimelteon at this dose.

Rosiglitazone (CYP2C8 substrate): Administration of tasimelteon capsules 20 mg once a day for 16 days did not produce any clinically significant changes in the Tmax, Cmax, or AUC of rosiglitazone after oral administration of 4 mg. This indicates that there is no induction of CYP2C8 by tasimelteon at this dose.

Effect of Alcohol on Tasimelteon

In a study of 28 healthy volunteers, a single dose of ethanol (0.6 g/kg for women and 0.7 g/kg for men) was co-administered with a 20 mg dose of tasimelteon. There was a trend for an additive effect of tasimelteon and ethanol on some psychomotor tests.

13 NONCLINICAL TOXICOLOGY

13.1 Carcinogenesis, Mutagenesis, Impairment of Fertility

Carcinogenesis

Tasimelteon was administered orally for up to two years to mice (30, 100, and 300 mg/kg/day) and rats (20, 100, and 250 mg/kg/day). No evidence of carcinogenic potential was observed in mice; the highest dose tested is approximately 75 times the maximum recommended human dose (MRHD) of 20 mg/day, based on a mg/m^2 body surface area. In rats, the incidence of liver tumors was increased in males (adenoma and carcinoma) and females (adenoma) at 100 and 250 mg/kg/day; the incidence of tumors of the uterus (endometrial adenocarcinoma) and uterus and cervix (squamous cell carcinoma) were increased at 250 mg/kg/day. There was no increase in tumors at the lowest dose tested in rats, which is approximately 10 times the MRHD based on a mg/m^2 body surface area.

Mutagenesis

Tasimelteon was negative in an in vitro bacterial reverse mutation (Ames) assay, an in vitro cytogenetics assay in primary human lymphocytes, and an in vivo micronucleus assay in rats.

Impairment of Fertility

When male and female rats were given tasimelteon at oral doses of 5, 50, or 500 mg/kg/day prior to and throughout mating and continuing in females to gestation day 7, estrus cycle disruption and decreased fertility were observed at all but the lowest dose tested. The no-effect dose for effects on female reproduction (5 mg/kg/day) is approximately 2 times the MRHD based on a mg/m^2 body surface area.

14 CLINICAL STUDIES

14.1 Non-24-Hour Sleep-Wake Disorder (Non-24)

The effectiveness of tasimelteon in the treatment of Non-24-Hour Sleep-Wake Disorder (Non-24) was established in two randomized double-masked, placebo-controlled, multicenter, parallel-group studies (Studies 1 and 2) in totally blind patients with Non-24.

In study 1, 84 patients with Non-24 (median age 54 years) were randomized to receive tasimelteon capsules 20 mg or placebo, one hour prior to bedtime, at the same time every night for up to 6 months.

Study 2 was a randomized withdrawal trial in 20 patients with Non-24 (median age 55 years) that was designed to evaluate the maintenance of efficacy of tasimelteon after 12-weeks. Patients were treated for approximately 12 weeks with tasimelteon capsules 20 mg one hour prior to bedtime, at the same time every night. Patients in whom the calculated time of peak melatonin level (melatonin acrophase) occurred at approximately the same time of day (in contrast to the expected daily delay) during the run-in phase were randomized to receive placebo or continue treatment with tasimelteon capsules 20 mg for 8 weeks.

Study 1 and Study 2 evaluated the duration and timing of nighttime sleep and daytime naps via patient-recorded diaries. During Study 1, patient diaries were recorded for an average of 88 days during screening, and 133 days during randomization. During Study 2, patient diaries were recorded for an average of 57 days during the run-in phase, and 59 days during the randomized-withdrawal phase.

Because symptoms of nighttime sleep disruption and daytime sleepiness are cyclical in patients with Non-24, with severity varying according to the state of alignment of the individual patient’s circadian rhythm with the 24-hour day (least severe when fully aligned, most severe when 12 hours out of alignment), efficacy endpoints for nighttime total sleep time and daytime nap duration were based on the 25% of nights with the least nighttime sleep, and the 25% of days with the most daytime nap time. In Study 1, patients in the tasimelteon group had, at baseline, an average 195 minutes of nighttime sleep and 137 minutes of daytime nap time on the 25% of most symptomatic nights and days, respectively. Treatment with tasimelteon resulted in a significant improvement, compared with placebo, for both of these endpoints in Study 1 and Study 2 (see Table 3).

Table 3: Effects of Tasimelteon Capsules 20 mg on Nighttime Sleep Time and Daytime Nap Time in Study 1 and Study 2

 | Study 1 |  | Study 2
Change from Baseline | Tasimelteon Capsules 20 MG N=42 | Placebo N=42 | Tasimelteon Capsules 20 MG N=10 | Placebo N=10
Nighttime sleep time on 25% most symptomatic nights (minutes) | 50 | 22 | -7 | -74
Daytime nap time on 25% most symptomatic days (minutes) | -49 | -22 | -9 | 50

A responder analysis of patients with both ≥ 45 minutes increase in nighttime sleep and ≥ 45 minutes decrease in daytime nap time was conducted in Study 1: 29% (n=12) of patients treated with tasimelteon, compared with 12% (n=5) of patients treated with placebo met the responder criteria.

16 HOW SUPPLIED/STORAGE AND HANDLING

Tasimelteon 20 mg capsules are available as hard gelatin capsules with dark blue, opaque body and dark blue, opaque cap. Imprinted “APO” and “TAS” over “20” in white ink.

Bottles of 30 NDC 60505-4665-3

Bottles of 90 NDC 60505-4665-9

Storage and Handling

Store tasimelteon capsules at 20°C to 25°C (68°F to 77°F); excursions permitted from 15°C to 30°C (59°F to 86°F) [see USP Controlled Room Temperature]. Protect from exposure to light and moisture.

17 PATIENT COUNSELING INFORMATION

- Advise patients to limit their activities to preparing for going to bed after taking tasimelteon capsules because tasimelteon can potentially impair the performance of activities requiring complete mental alertness [see Warnings and Precautions (5.1)].
- Administration Information for tasimelteon capsules [see Dosage and Administration (2.1, 2.2, 2.4)].
  - Advise patients to take tasimelteon capsules without food.
  - Advise patients to take tasimelteon capsules before bedtime at the same time every night.
  - Advise patients to skip the dose that night if they cannot take tasimelteon capsules at approximately the same time on a given night.
  - Advise patients to swallow tasimelteon capsules whole.
- Non-24 (tasimelteon capsules)
  Advise patients that because of individual differences in circadian rhythms, daily use for several weeks or months may be necessary before benefit from tasimelteon capsules is observed [see Dosage and Administration (2.2)].

APOTEX INC.

TASIMELTEON CAPSULES

20 mg

Manufactured By
Apotex Inc.
Toronto, Ontario
Canada M9L 1T9

Manufactured For
Apotex Corp.
Weston, Florida
USA 33326

Rev. 5

PRINCIPAL DISPLAY PANEL 20 mg 30s

Representative sample of labeling (see HOW SUPPLIED section of complete listing):

APOTEX CORP. NDC 60505-4665-3

Tasimelteon Capsules 20 mg 30 counts

Rx only